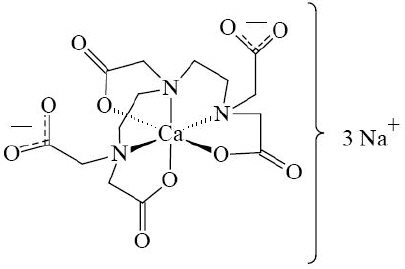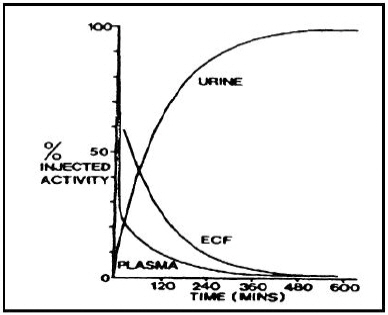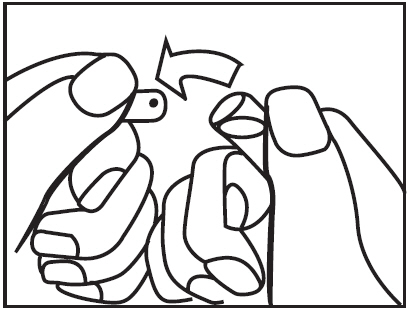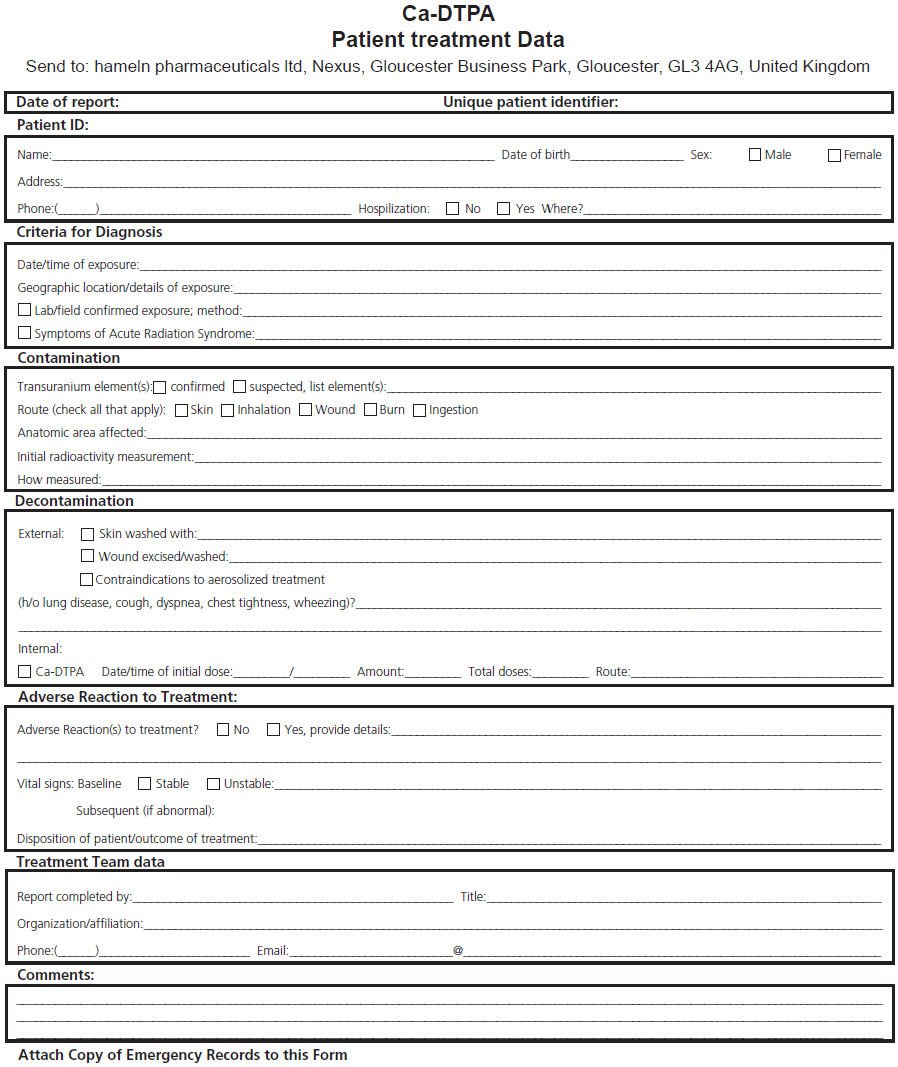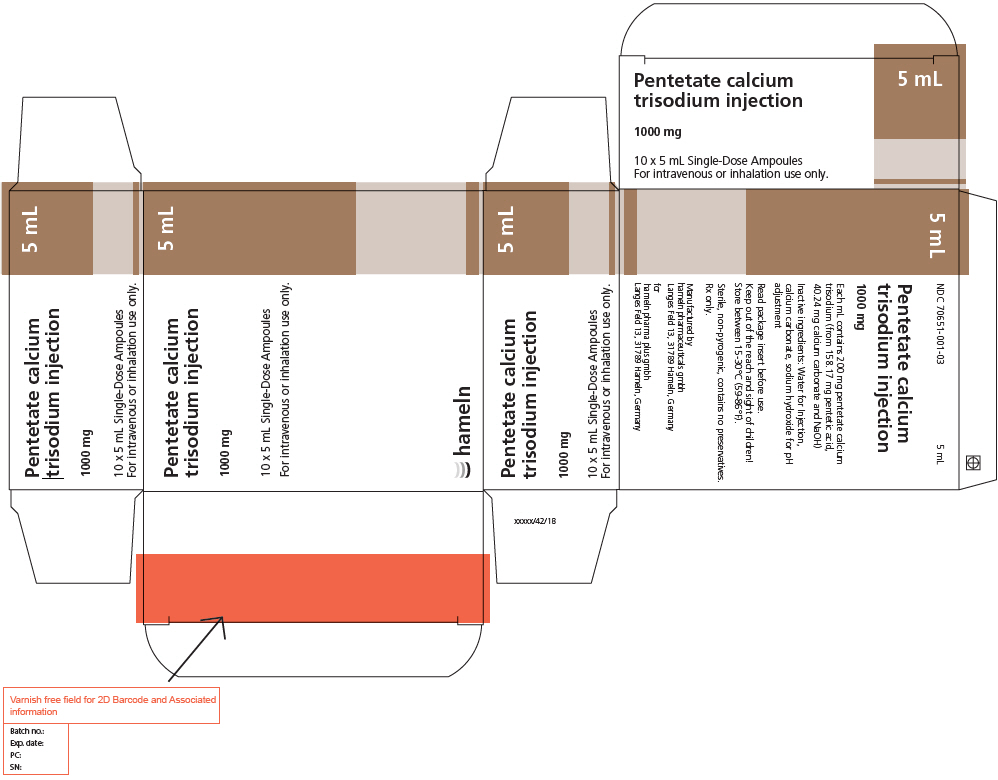 DRUG LABEL: Pentetate calcium trisodium
NDC: 70651-001 | Form: INJECTION, SOLUTION, CONCENTRATE
Manufacturer: hameln pharma gmbh
Category: prescription | Type: HUMAN PRESCRIPTION DRUG LABEL
Date: 20210106

ACTIVE INGREDIENTS: pentetate calcium trisodium 1000 mg/5 mL
INACTIVE INGREDIENTS: Water; Sodium hydroxide; Calcium carbonate

HIGHLIGHTS OF PRESCRIBING INFORMATION

These highlights do not include all the information needed to use PENTETATE CALCIUM TRISODIUM INJECTION safely and effectively.
See full prescribing information for PENTETATE CALCIUM TRISODIUM INJECTION.
Pentetate calcium trisodium injection (Ca-DTPA)
For intravenous or inhalation administration
Initial U.S. Approval: 2004

WARNING: ASTHMA EXACERBATION WITH NEBULIZATION and DEPLETION OF TRACE METALS DURING THERAPY

See full prescribing information for complete boxed warning.

- Nebulized Ca-DTPA may be associated with asthma exacerbation. (5.1)
- Ca-DTPA is associated with depletion of trace metals such as zinc. The magnitude of depletion increases with split daily dosing, with increasing dose and with increased treatment duration. Only a single dose of Ca-DTPA is recommended. Use Zn-DTPA if additional chelation therapy is indicated. Monitor serum zinc levels, serum creatinine, BUN, electrolytes, urinalysis and blood cell counts during Ca-DTPA or Zn-DTPA therapy. (2.4, 5.2)

1 INDICATIONS AND USAGE

Pentetate calcium trisodium injection is a radiomitigation chelator indicated for treatment of individuals with known or suspected internal contamination with plutonium, americium, or curium to increase the rates of elimination. (1)

2 DOSAGE AND ADMINISTRATION

Chelation treatment is most effective if administered within the first 24 hours. (2.1, 2.2)

In adults and adolescents, administer intravenously a single 1.0 gram Ca-DTPA dose. (2.1)

In children less than 12 years of age, administer intravenously, a single 14 mg/kg Ca-DTPA dose, not to exceed 1.0 gram. (2.1)

Zn-DTPA is recommended for maintenance chelation therapy after the first 24 hours. If Zn-DTPA is unavailable, chelation therapy may continue with Ca-DTPA. (2.1)

See Full Prescribing Information for dose (2.1) and nebulized chelation therapy (2.3)

3 DOSAGE FORMS AND STRENGTHS

1000 mg / 5 mL single-use ampoules (3)

4 CONTRAINDICATIONS

None (4)

5 WARNINGS AND PRECAUTIONS

- Nebulized Ca-DTPA may be associated with exacerbation of asthma. Monitor patients for signs and symptoms of asthma exacerbation when administering Ca-DTPA by the inhalation route. (5.1)
- Ca-DTPA is associated with depletion of endogenous trace metals (e.g., zinc, magnesium, manganese). (5.2)
- Take appropriate safety measures to minimize contamination of care-takers by contaminated body fluids. (5.3)
- Use Ca-DTPA with caution in individuals with severe hemochromatosis. (5.4)

6 ADVERSE REACTIONS

There is limited experience with Ca-DTPA. Adverse events included headache, lightheadedness, chest pain, allergic reaction, dermatitis, metallic taste, nausea and diarrhea, and injection site reactions. (6)

To report SUSPECTED ADVERSE REACTIONS, contact the hameln Pharmacovigilance Department at +44 (0) 7706 210 133 or drugsafety@hameln.co.uk or FDA at 1-800-FDA-1088 or www.fda.gov/medwatch.

7 DRUG INTERACTIONS

Adequate and well-controlled drug-drug interaction studies in humans were not identified in the literature. (7)

8 USE IN SPECIFIC POPULATIONS

- Pregnancy: Based on animal data, Ca-DTPA may cause fetal harm. Chelation treatment of pregnant women should begin and continue with Zn-DTPA. If Zn-DTPA is not available, Ca-DTPA should be used. (8.1)
- Nursing Mothers: Women with known or suspected internal contamination with radiocontaminants should not breast feed, whether or not they are receiving chelation therapy. (5.3, 8.3)
- Pediatric Use: Safety and effectiveness of intravenous Ca-DTPA were extrapolated from adults. Safety and effectiveness of the nebulized route of administration have not been established. (8.4)

FULL PRESCRIBING INFORMATION

WARNING: ASTHMA EXACERBATION WITH NEBULIZATION and DEPLETION OF TRACE METALS DURING THERAPY

- Nebulized Ca-DTPA may be associated with asthma exacerbation. (5.1)
- Ca-DTPA is associated with depletion of trace metals such as zinc. The magnitude of depletion increases with split daily dosing, with increasing dose and with increased treatment duration. Only a single dose of Ca-DTPA is recommended. Use Zn-DTPA if additional chelation therapy is indicated. Monitor serum zinc levels, serum creatinine, BUN, electrolytes, urinalysis and blood cell counts during Ca-DTPA or Zn-DTPA therapy. (2.4, 5.2)

1 INDICATIONS AND USAGE

Ca-DTPA is indicated for treatment of individuals with known or suspected internal contamination with plutonium, americium, or curium to increase the rates of elimination.

2 DOSAGE AND ADMINISTRATION

2.1 Dose

Administer Ca-DTPA as the initial dose during the first 24 hours after internal contamination. Ca-DTPA is more effective than Zn-DTPA during this time period. If Ca-DTPA is not available, use Zn-DTPA as the initial therapy. On the next day, if additional chelation therapy is indicated, begin daily treatment with Zn-DTPA (see Zn-DTPA labeling). If Zn-DTPA is not available, chelation therapy may continue with Ca-DTPA; concomitant mineral supplements containing zinc should be given. [See Warnings and Precautions (5.2)]

Do not administer more than one dose per 24 hour period.

Adults and Adolescents

A single 1.0 gram initial dose of Ca-DTPA administered intravenously.

Children less than 12 years of age

A single 14 mg/kg initial dose of Ca-DTPA administered intravenously, not to exceed 1.0 gram.

If Zn-DTPA is not available

For adults and adolescents, the recommended maintenance dose is 1.0 gram Ca-DTPA once daily administered intravenously. For children less than 12 years of age, the recommended maintenance dose is 14 mg/kg Ca-DTPA once daily administered intravenously, not to exceed 1.0 gram per day.

Renally Impaired Patients

No dose adjustment is needed. However, renal impairment may reduce the rate at which chelators remove radiocontaminants from the body. In heavily contaminated patients with renal impairment, dialysis may be used to increase the rate of elimination. High efficiency high flux dialysis is recommended. Because dialysis fluid will become radioactive, radiation precautions must be taken to protect personnel, other patients, and the general public.

2.2 General

Chelation treatment is most effective if administered within the first 24 hours after internal contamination. Start chelation treatment as soon as possible after suspected or known internal contamination. When treatment cannot be started right away, give chelation treatment as soon as it becomes available. Chelation treatment is still effective even after time has elapsed following internal contamination. The chelating effects of Ca-DTPA are greatest when radiocontaminants are still circulating or are in interstitial fluids. The effectiveness of chelation decreases with time following internal contamination as the radiocontaminants become sequestered in liver and bone.

If internal contamination with radiocontaminants other than plutonium, americium, or curium, or unknown radiocontaminants is suspected, additional therapies may be needed (e.g., Prussian blue, potassium iodide).

2.3 Methods of Administration

Use intravenous administration of Ca-DTPA if the route of internal contamination is not known or if multiple routes of internal contamination are likely. Administer Ca-DTPA solution (1 gram in 5 mL) either with a slow intravenous push over a period of 3-4 minutes or by intravenous infusion diluted in 100-250 mL of 5% dextrose in water (D5W), Ringers Lactate, or Normal Saline.

In individuals whose internal contamination is only by inhalation within the preceding 24 hours, Ca-DTPA can be administered by nebulized inhalation as an alternative route of administration. Dilute Ca-DTPA for nebulization at a 1:1 ratio with sterile water or saline. After nebulization, encourage patients to avoid swallowing any expectorant. Some individuals may experience respiratory adverse events after inhalation therapy. [See Warnings and Precautions (5.1)]

The safety and effectiveness of the nebulized route of administration have not been established in the pediatric population.

The safety and effectiveness of the intramuscular route of injection have not been established. [See Overdosage (10)]

2.4 Monitoring

When possible, obtain baseline blood and urine samples (CBC with differential, serum creatinine, BUN and electrolytes, urinalysis, and blood and urine radioassays) before initiating treatment.

Ca-DTPA must be given with very careful monitoring of serum zinc and complete blood counts. When appropriate, administer vitamin or mineral supplements that contain zinc. [See Warnings and Precautions (5.2)]

To establish an elimination curve, obtain a quantitative baseline estimate of the total internalized transuranium element(s) and measures of elimination of radioactivity by appropriate whole-body counting, by bioassay (e.g., biodosimetry), or fecal/urine sample whenever possible.

During Treatment

- Measure the radioactivity in blood, urine, and fecal samples weekly to monitor the radioactive contaminant elimination rate.
- Monitor CBC with differential, BUN, serum creatinine and electrolytes, and urinalysis. If the individual is receiving more than one dose of Ca-DTPA, consider mineral supplementation as appropriate based on these laboratory tests.
- Record any adverse events from Ca-DTPA.

3 DOSAGE FORMS AND STRENGTHS

1000 mg / 5 mL single-use ampoules.

4 CONTRAINDICATIONS

None.

5 WARNINGS AND PRECAUTIONS

5.1 Asthma Exacerbation

Nebulized Ca-DTPA is associated with asthma exacerbation. Monitor patients for signs and symptoms of asthma exacerbation when administering Ca-DTPA by the inhalation route. [See Adverse Reactions (6)]

5.2 Depletion of Body Trace Mineral Stores

Ca-DTPA is associated with depletion of endogenous trace metals (e.g., zinc, magnesium, manganese). The magnitude of depletion increases with split daily dosing, with increasing dose, and with increased treatment duration. [See Clinical Pharmacology (12.3)] Only a single initial dose of Ca-DTPA is recommended. Use Zn-DTPA if additional chelation therapy is indicated (See Zn-DTPA labeling). If Zn-DTPA is not available, chelation therapy may continue with Ca-DTPA but give mineral supplements containing zinc concomitantly, as appropriate.

Monitor serum zinc levels, electrolytes and blood cell counts during Ca-DTPA or Zn-DTPA therapy. Give mineral or vitamin plus mineral supplements that contain zinc as appropriate. [See Dosage and Administration (2.4)]

5.3 Risks to Care-takers

Radioactive metals are known to be excreted in the urine, feces, and breast milk. In individuals with recent internal contamination with plutonium, americium, or curium, Ca-DTPA treatment increases excretion of radioactivity in the urine. Take appropriate safety measures to minimize contamination of others. [See Patient Counseling Information (17)]

5.4 Risks for Patients with Hemochromatosis

Use of only a single Ca-DTPA dose is particularly important for patients with hemochromatosis. Deaths have been reported in patients with severe hemochromatosis who received Ca-DTPA for more than 1 day, by intramuscular injection. [See Overdosage (10)]

6 ADVERSE REACTIONS

In the U.S. Registry, a total of 646 individuals received at least one dose of either Ca-DTPA or Zn-DTPA. Of these, 632 received Ca-DTPA by one or more routes of administration. Three hundred and twenty-six individuals were dosed by inhalation, 293 by intravenous injection, and 60 by other or unknown routes of administration.

Of the individuals that received Ca-DTPA, 393/632 (62%) received one dose and 65 (10%) received two doses. The remaining 174 individuals received three or more doses. The largest number of Ca-DTPA doses to a single individual was 338 delivered over 6.5 years. Overall, the presence or absence of adverse events was recorded in 310/646 individuals. Of these 19 (6.1%) individuals reported at least one adverse event. The total number of recorded adverse events was 20. Of the 20 adverse events, 18 adverse events occurred after treatment with Ca-DTPA. Adverse events included headache, lightheadedness, chest pain, allergic reaction, dermatitis, metallic taste, nausea and diarrhea, and injection site reactions.

Cough and/or wheezing were experienced by 2 individuals receiving nebulized Ca-DTPA, one of whom had a history of asthma.

In literature reports, prolonged treatment with Ca-DTPA resulted in depletion of zinc, magnesium, manganese and possibly metalloproteinases. [See Warnings and Precautions (5.2)]

7 DRUG INTERACTIONS

Adequate and well-controlled drug-drug interaction studies in humans were not identified in the literature. When an individual is contaminated with multiple radiocontaminants, or when the radiocontaminants are unknown, additional therapies may be needed (e.g., Prussian blue, potassium iodide).

8 USE IN SPECIFIC POPULATIONS

8.1 Pregnancy

TERATOGENIC EFFECTS

Pregnancy Category C

Risk Summary

There are no adequate and well-controlled studies of Ca-DTPA use in pregnant women. Ca-DTPA chelation therapy causes depletion of body stores of zinc, a trace metal essential for fetal development [see Warnings and Precautions (5.2)]. The consequences of zinc depletion and results of animal studies suggest a teratogenic risk in humans. Ca-DTPA was teratogenic and embryotoxic in mice at daily doses 2 to 8 times the recommended daily human dose, based on body surface area (BSA), with a dose-dependent increase in the frequency of gross malformations. Ca-DTPA was teratogenic in dogs at approximately half the recommended daily human dose based on BSA, as described below. There are no animal or human data evaluating the teratogenic effect of a single dose of Ca-DTPA. Ca-DTPA should be used during pregnancy only if the potential benefit justifies the potential risk to the fetus.

Clinical Considerations

Chelation treatment of pregnant women should begin and continue with Zn-DTPA, if available, except in cases of high internal radioactive contamination. Because Ca-DTPA is more effective than Zn-DTPA in the first 24 hours after internal contamination, it may be appropriate to use a single dose of Ca-DTPA with vitamin or mineral supplements that contain zinc as the initial treatment.

Animal Data

Ca-DTPA is teratogenic and embryotoxic in mice during any period of gestation following five daily subcutaneous injections of 720 to 2880 micromol Ca-DTPA/kg [2 to 8 times the recommended daily human dose of 1 gram based on BSA]. The frequency of gross malformations (e.g., exencephaly, spina bifida, cleft palate, ablepharia, and polydactyly) and fetal mortality increased with dose, with higher susceptibility in early and mid gestation. Five daily doses of 360 micromol Ca-DTPA/kg in mice, approximately equivalent to the recommended daily human dose (based on BSA) produced no harmful effects. A study of two pregnant dogs given daily intravenous injections of 30 micromol Ca-DTPA/kg (approximately half the recommended daily human dose based on BSA) from implantation until parturition showed severe teratogenic effects (brain damage), and decrease in the number of surviving pups.

8.3 Nursing mothers

It is not known whether Ca-DTPA is excreted in human milk. Radiocontaminants are known to be excreted in breast milk. Women with known or suspected internal contamination with radiocontaminants should not breast feed, whether or not they are receiving chelation therapy. Precautions should be taken when discarding breast milk. [See Warnings and Precautions (5.3)]

8.4 Pediatric use

The safety and effectiveness of Ca-DTPA were established in the adult population and efficacy was extrapolated to the pediatric population for the intravenous route based on the comparability of pathophysiologic mechanisms. The dose is based on body size adjustment for an intravenous drug that is renally cleared [See Dosage and Administration (2.1)]. The safety and effectiveness of the nebulized route of administration have not been established in the pediatric population.

10 OVERDOSAGE

In previous clinical studies, three deaths were reported in patients with severe hemochromatosis who were treated with daily intramuscular Ca-DTPA dosed up to 4 gram per day to reduce iron stores. One patient became comatose and died after receiving a total of 14 grams Ca-DTPA, and the other two died after two weeks of daily treatment. Causal association with these events and the drug has not been established. [See Warnings and Precautions (5.4)]

11 DESCRIPTION

Pentetate calcium trisodium injection contains the sodium salt of calcium diethylenetriaminepentaacetate. Pentetate calcium trisodium is also known as trisodium calcium diethylenetriaminepentaacetate and is commonly referred to as Ca-DTPA. It has a molecular formula of Na3CaC14H18N3O10 and a molecular weight of 497.4 Daltons. It is represented by the following structural formula:

Ca-DTPA is supplied as a clear, colorless, hyperosmolar (1260 mOsmol/kg) solution in a colorless ampoule containing 5 mL. The ampoule contents are sterile, non-pyrogenic and suitable for intravenous administration. Each mL of solution contains the equivalent of 200 mg pentetate calcium trisodium (obtained from 158.17 mg pentetic acid, 40.24 mg calcium carbonate and NaOH) in water for injection, USP. The pH of the solution is adjusted with NaOH and is between 7.3-8.3.

12 CLINICAL PHARMACOLOGY

12.1 Mechanism of Action

Ca-DTPA forms stable chelates with metal ions by exchanging calcium for a metal of greater binding capacity. The radioactive chelates are then excreted by glomerular filtration into the urine. In animal studies, Ca-DTPA forms less stable chelates with uranium and neptunium in vivo resulting in the deposition of these elements in tissues including the bone. Ca-DTPA treatments are not expected to be effective for uranium and neptunium. Radioactive iodine is not bound by DTPA.

12.2 Pharmacodynamics

In a study of rodents internally contaminated with plutonium, the rate of plutonium elimination was measured after treatment with Ca-DTPA and Zn-DTPA given intravenously as a single dose of 10 to 1,000 micromol/kg (0.54-54 × maximum human dose, MHD). When treated within one hour of internal contamination, Ca-DTPA resulted in about a 10-fold higher rate of elimination of plutonium in the urine as compared to Zn-DTPA. The chelating capacity of Ca-DTPA is greatest immediately and up to approximately 24 hours after internal contamination, a time period when the radiocontaminant is still circulating and readily available for chelation. After the first dose of Ca-DTPA, maintenance treatment with either Ca-DTPA or Zn-DTPA resulted in similar rates of elimination of radioactivity. However, at comparable doses, Ca-DTPA had more toxicity (e.g., more depletion of trace metals, higher rate of mortality, the presence of kidney and liver vacuolization, and small bowel hemorrhagic lesions).

In another study, rodents contaminated with aerosolized plutonium and americium were treated with Ca-DTPA and Zn-DTPA. The treatment schedule involved inhalation of Ca-DTPA 2 micromol/kg (0.11 MHD) 30 minutes after contamination followed by inhalation of Zn-DTPA 2 micromol/kg at approximately 6 hours, 1, 2, 3, and 6 days, then twice weekly to day 26 or day 27. The treatment regime reduced the lung deposit of plutonium and americium to 1-2% of that in untreated animals. Systemic deposit in liver and skeleton were reduced by half.

Literature and U.S. Registry data in humans indicate that intravenous administration of Ca-DTPA forms chelates with radioactive contaminants found in the circulation, interstitial fluid, and tissues. When Ca-DTPA is administered by inhalation within 24 hours of internal radioactive contamination, it can chelate transuranium elements. Expectoration is expected to decrease the amount of radioactive contaminant available for systemic absorption.

The effectiveness of chelation decreases with time after internal contamination because the transuranium elements become incorporated into the tissues. Give chelation treatment as soon as possible after known or suspected internal contamination with transuranium elements has occurred. [See Dosage and Administration (2.1, 2.2)]

12.3 Pharmacokinetics

Plasma retention and urinary excretion data were obtained in 2 subjects that received 750 kBq of ^14C-DTPA. As shown in Figure 1, the radiolabeled DTPA was rapidly distributed throughout the extracellular fluid space and was cleared by glomerular filtration. The plasma retention up to 7 hours post dosing was expressed by the sum of three exponential components with average half-lives of 1.4 min, 14.5 min, and 94.4 min. The level of activity in the plasma was below the limit of detection 24 hours after injection. During the study, no detectable activity was exhaled or excreted in the feces. By 24 hours, cumulative urinary excretion was more than 99% of the injected dose.

Figure 1: Percent of ^14C-DTPA Distribution

Absorption

Ca-DTPA is poorly absorbed in the gastrointestinal tract. In animal studies, after oral administration, absorption was approximately 5%. In a U.S. Registry of 18 patients who received a single inhaled or intravenous dose of 1 gram, urine data indicate that the inhaled product was absorbed and resulted in a comparable elimination of the radiocontaminant. One study of 2 human subjects that received Ca-DTPA with ^14C-DTPA by inhalation revealed approximately 20% absorption from the lungs. Human or animal bioavailability comparisons for Ca-DTPA are not available after administration by inhalation and intravenous injection. [See Clinical Studies (14)]

Distribution

Following intravenous administration, Ca-DTPA is rapidly distributed throughout the extracellular fluid space. No significant amount of Ca-DTPA penetrates into erythrocytes or other cells. No accumulation of Ca-DTPA in specific organs has been observed. There is little or no binding of the chelating agent by the renal parenchyma.

Metabolism

Ca-DTPA undergoes a minimal amount of metabolic change in the body.

Adverse Metabolic Effects

Studies in animals and humans showed that Ca-DTPA binds endogenous metals of the body (i.e., zinc (Zn), magnesium (Mg) and manganese (Mn)). In an animal study, high doses of Ca-DTPA led to the loss of zinc and manganese mainly from the small intestine, skeleton, pancreas, and testes. Dosing over several days resulted in mobilization or binding of endogenous metals in exchange for calcium and a consequent impairment of metal-controlled or activated systems. The rate and amount of endogenous metal depletion increased with split daily dosing and with the length of treatment. Depletion of these endogenous metals can interfere with necessary mitotic cellular processes. Over longer time periods, depletion of zinc due to Ca-DTPA therapy may result in transient inhibition of a metalloenzyme-δ-aminolevulinic acid dehydrase (ALAD) in the blood and suppressed hematopoiesis.

Elimination

Ca-DTPA is cleared from the plasma in the first few hours after dosing through urinary excretion by glomerular filtration. Renal tubular excretion has not been documented. In stool samples tested, only a very small amount of radioactivity (<3%) was detected.

Renal Impaired and/or Compromised Liver Function Patients

Adequate and well-controlled pharmacokinetic and pharmacodynamic studies in renally impaired and/or hepatically impaired patients were not identified in the literature. Both Ca-DTPA and its radioactive chelates are excreted by glomerular filtration. Impaired renal function may decrease their rates of elimination and increase the serum half-life of Ca-DTPA.

13 NONCLINICAL TOXICOLOGY

13.1 Carcinogenesis, Mutagenesis, Impairment of Fertility

Studies with Ca-DTPA to evaluate carcinogenesis, mutagenesis, and impairment of fertility have not been performed. Data for Ca-DTPA effects on spermatogenesis are not available.

13.2 Animal Toxicology and/or Pharmacology

[See Clinical Pharmacology (12)]

14 CLINICAL STUDIES

All clinical data has come from the treatment of individuals who were accidentally contaminated. Observational data were maintained in a U.S. Registry of individuals with internal radioactive contamination primarily from acute occupational contamination with plutonium, americium, and curium.

In 286 individuals, bioassays were available to measure urinary radioactivity elimination after chelation therapy. Of these 286 individuals, 18 had matched pre- and post-chelator urine radioactivity bioassay results available. Seventeen of these individuals received 1 gram of Ca-DTPA as the first dose. Of these, 9 individuals received the first dose by nebulization (1:1 Ca-DTPA and saline) and 8 received Ca-DTPA intravenously. The elimination of radiocontaminants was measured using the ratio of the urine radioactivity before treatment to the maximum urine radioactivity after treatment (the excretion enhancement factor, EEF). As shown in Table 1, after one dose, the mean EEF was 25.7. The descriptive results and variability for the intravenous, inhaled, and combined routes are considered to be similar.

Table 1: Urine Excretion Enhancement Factor (EEF) of Transuranium Elements after an Initial Dose of 1g (Ca-DTPA, N=17)
Results | Intravenous | Inhaled | Combined Routes
Mean | 25.9 | 25.4 | 25.7
Median | 12.5 | 19.3 | 12.8
SD | 33.8 | 28.2 | 30.1
Range | 1.1-396.1 | 0.5-80.0 | 0.5-396.1

After initial treatment with Ca-DTPA, maintenance treatment was continued with 1 gram Zn-DTPA doses over a period of days, months or years, depending upon the extent of internal contamination and individual response to therapy. Most patients received a single dose of Ca-DTPA. The longest treatment duration was approximately 6.5 years. Similar increases in urinary radioactivity elimination following chelator administration were supported by data from the remaining 268 individuals in the U.S. Registry and from the literature.

16 HOW SUPPLIED/STORAGE AND HANDLING

Ca-DTPA is supplied as a sterile solution in 5 mL single-use clear glass ampoules at a concentration of 200 mg/mL for intravenous use. Each ampoule contains the equivalent of 1000 mg of pentetate calcium trisodium.

NDC 70651-001-03: | 5 mL single-dose ampoules, package of 10.

16.2 Storage

Store between 15-30°C (59-86°F).

16.3 Handling

Inspect parenteral drug products visually for particulate matter and discoloration prior to administration, whenever solution and container permit. The product may be filtered using a sterile filter if particles are seen subsequent to opening of the ampoule.

OPC ampoule: to open, turn so that the point faces upward and break off the neck with a downward movement.

17 PATIENT COUNSELING INFORMATION

Instruct patients to:

- drink plenty of fluids and void frequently to promote dilution of the radioactive chelate in the urine and minimize radiation exposure directly to the bladder.
- use a toilet instead of a urinal, and flush several times after each use.
- clean up spilled urine or feces completely and wash hands thoroughly. Wash clothing or linens separately if blood or urine comes in contact.
- dispose of any expectorant carefully. Avoid swallowing the expectorant if possible.

Instruct parents and child-care givers to take extra precaution in handling the urine, feces, and expectorants of children to avoid any additional exposure to either the care-giver or to the child.

Instruct nursing mothers to take extra precaution in disposing of breast milk. [See Use in Specific Populations (8.3)]

18 COLLECTION OF PATIENT TREATMENT DATA

To develop long-term response data and information on the risk of developing late malignancy, provide detailed information on patient treatment to the manufacturer (see Patient Treatment Data Form). In case you need additional forms, please use the enclosed form as a template or see the following website: www.ca-dtpa.com. Include a record of the radioactive body burden and bioassay results at defined time intervals, a description of measurement methods to facilitate analysis of data, and adverse events.

Questions regarding the use of Ca-DTPA for the treatment of internal contamination with transuranium elements may be referred to:

hameln pharmaceuticals ltd
Nexus
Gloucester Business Park
Gloucester, GL3 4AG
United Kingdom
Tel: + 44 / 1452 / 621661
Fax: +44 / 1452 / 632732
e-mail: drugsafety@hameln.co.uk

Contact person: Richard Wysocki
Phone: +44 / 1452 / 621661
Fax: +44 / 1452 / 632732
Email: r.wysocki@hameln.co.uk

Revised: 10/2016

44641/17/16

PRINCIPAL DISPLAY PANEL - 5 mL Ampoule Package

Pentetate calcium
trisodium injection

5 mL

1000 mg

10 x 5 mL Single-Dose Ampoules
For intravenous or inhalation use only.

hameln